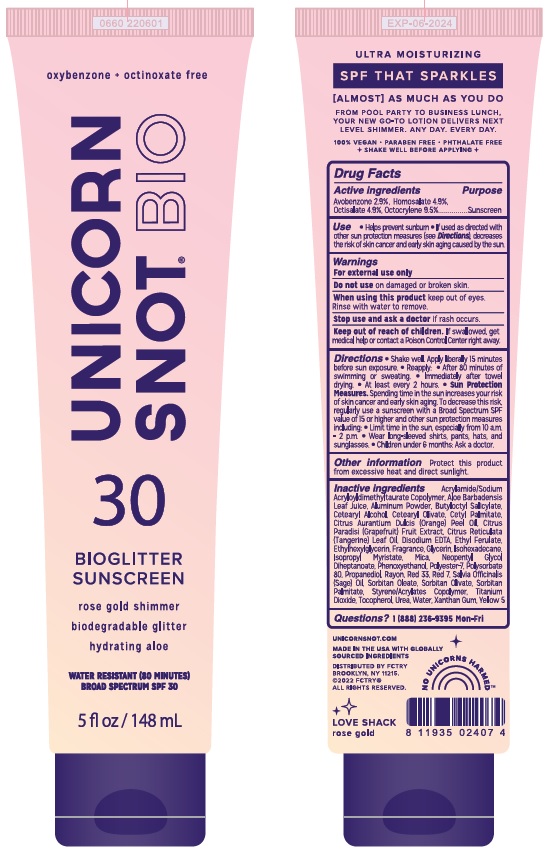 DRUG LABEL: Unicorn Snot Bio 30
NDC: 72192-023 | Form: LOTION
Manufacturer: Jailbreak Toys, INC.
Category: otc | Type: HUMAN OTC DRUG LABEL
Date: 20220426

ACTIVE INGREDIENTS: AVOBENZONE 2.9 g/100 mL; OCTISALATE 4.9 g/100 mL; OCTOCRYLENE 9.5 g/100 mL; HOMOSALATE 4.9 g/100 mL
INACTIVE INGREDIENTS: SODIUM ACRYLATE/SODIUM ACRYLOYLDIMETHYLTAURATE COPOLYMER (4000000 MW); POLYESTER-7; D&C RED NO. 7; SORBITAN MONOOLEATE; SORBITAN OLIVATE; .ALPHA.-TOCOPHEROL ACETATE; REGENERATED CELLULOSE; ISOHEXADECANE; PHENOXYETHANOL; POLYSORBATE 80; SAGE OIL; SORBITAN MONOPALMITATE; STYRENE/ACRYLAMIDE COPOLYMER (MW 500000); TITANIUM DIOXIDE; CETOSTEARYL ALCOHOL; CETEARYL OLIVATE; PROPANEDIOL; UREA; ETHYLHEXYLGLYCERIN; CETYL PALMITATE; ORANGE OIL; ETHYL FERULATE; MICA; GRAPEFRUIT; CITRUS RETICULATA LEAF OIL; GLYCERIN; NEOPENTYL GLYCOL DIHEPTANOATE; ISOPROPYL MYRISTATE; ALOE VERA LEAF; ALUMINUM; D&C RED NO. 33; WATER; BUTYLOCTYL SALICYLATE; XANTHAN GUM; EDETATE DISODIUM; FD&C YELLOW NO. 5

UNICORN SNOT BIO SPF 30 BIO GLITTER SUNSCREEN LOVE SHACK

Drug Facts

Active ingredients

Avobenzone 2.9%, Homosalate 4.9%, Octislate 4.9%, Octocrylene 9.5%

Purpose

Sunscreen

Use

- Helps prevent sunburn
- If used as directed with other sun protection measures (see Directions), decreases the risk of skin cancer adn early skin aging caused by the sun.

Warnings

For external use only

Do not use on damaged or broken skin.

When using this product keep out of eyes. Rinse with water to remove.

Stop use and ask doctor if rash occurs.

Keep out of reach of children. If swallowed, get medical help or contact a Poison Control Center right away.

Directions:

- Shake well. Apply liberally 15 minutes before sun exposure.
- Reapply:
- After 80 minutes of swimming or sweating
- Immediately after towel drying
- At least every 2 hours
- Sun Protection Measures. Spending time in the sun increases your risk of skin cancer and early skin aging. To decrease this risk, regularly use a sunscreen with a Broad Spectrum SPF value of 15 or higher and other sun protection measures including
- Limit time in the sun, especially from 10 a.m. - 2 p.m.
- Wear long-sleeved shirts, pants, hats and sunglasses.
- Children under 6 months: Ask a doctor.

Other information Protect this product from excessive heat and direct sunlight.

INACTIVE INGREDIENT

Inactive ingredients Acrylamide/Sodium Acryloyldimethyltaurate Copolymer, Aloe Barbadensis Leaf Juice, Aluminum Powder, Butyloctyl Salicylate, Cetearyl Alcohol, Cetearyl Olivate, Cetyl Palmitate, Citrus Aurantium Dulcis (Orange) Peel Oil, Citrus Paradisi (Grapefruit) Fruit Extract, Citrus Reticulata (Tangerine) Leaf Oil, Disodium EDTA, Ethyl Ferulate, Ethylhexylglycerin, Fragrance, Glycerin, Isohexadecane, Isopropyl Myristate, Mica, Neopentyl Glycol Diheptanoate, Phenoxyethanol, Polyester-7, Polysorbate 80, Propanediol, Rayon, Red 33, Red 7, Salvia Officinalis (Sage) Oil, Sorbitan Oleate, Sorbitan Olivate, Sorbitan Palmitate, Styrene/Acrylates Copolymer, Titanium Dioxide, Tocopherol, Urea, Water, Xanthan Gum, Yellow 5.

Questions? 1 (888) 236-9395 Mon - Fri

MADE IN THE USA WITH GLOBALLY SOURCED INGREDIENTS

Distributed by FCTRY

Brooklyn, NY 11215

LOVE SHACK

rose gold

PACKAGE LABEL

oxybenzone + octinoxate free

UNICORN SNOT BIO 30

BIOGLITTER SUNSCREEN

rose gold shimmer

biodegradable glitter

hydrating aloe

WATER RESISTANT (80 MINUTES)

BROAD SPECTRUM SPF 30

5 FL OZ / 148 mL